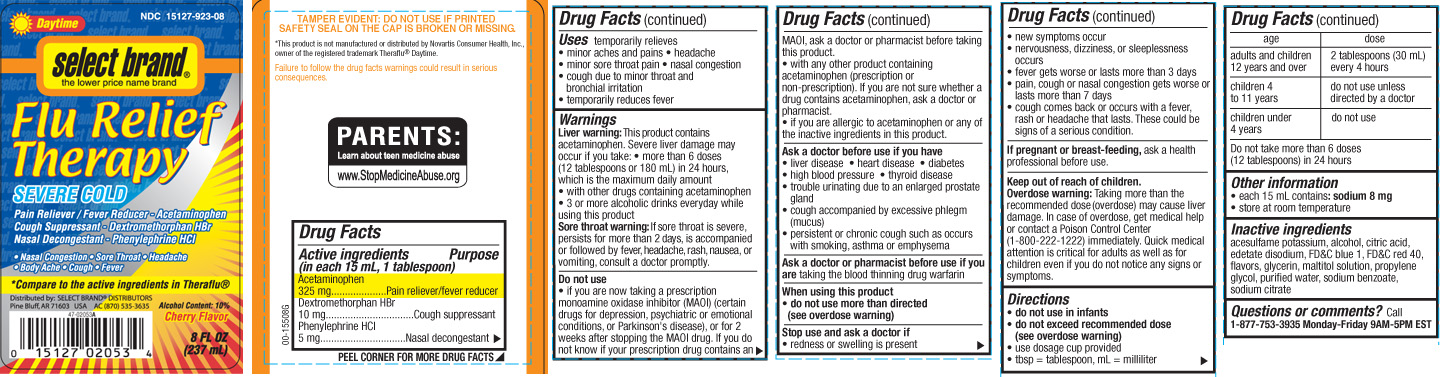 DRUG LABEL: Flu Relief Therapy Daytime
NDC: 15127-923 | Form: LIQUID
Manufacturer: Select Brand Dist.
Category: otc | Type: HUMAN OTC DRUG LABEL
Date: 20141020

ACTIVE INGREDIENTS: ACETAMINOPHEN 325 mg/1 1; DEXTROMETHORPHAN HYDROBROMIDE 10 mg/1 1; PHENYLEPHRINE HYDROCHLORIDE 5 mg/1 1
INACTIVE INGREDIENTS: ACESULFAME POTASSIUM; ALCOHOL; ANHYDROUS CITRIC ACID; EDETATE DISODIUM; FD&C BLUE NO. 1; FD&C RED NO. 40; GLYCERIN; MALTITOL; PROPYLENE GLYCOL; WATER; SODIUM BENZOATE; TRISODIUM CITRATE DIHYDRATE

Drug Facts

Active ingredients (in each 15 mL, 1 tablesoon)

Acetaminophen 325 mg

Dextromethorphan HBr 10 mg

Phenylephrine HCl 5 mg

Purpose

Pain reliever/fever reducer

Cough suppressant

Nasal decongestant

Uses

- temporarily relieves
  - minor aches and pains
  - headache
  - minor sore throat pain
  - nasal congestion
  - cough due to minor throat and bronchial irritation
  - temporarily reduces fever

Warnings

Liver warning: This product contains acetaminophen. Severe liver damage may occur if you take:

- more than 6 doses (12 tablespoons or 180 mL) in 24 hours, which is the maximum daily amount
- with other drugs containing acetaminophen
- 3 or more alcoholic drinks every day while using this product

Sore throat warning: If sore throat is severe, persists for more than 2 days, is accompanied or followed by fever, headache, rash, nausea, or vomiting, consult a doctor promptly.

Do not use

- if you are now taking a prescription monoamine oxidase inhibitor (MAOI) (certain drugs for depression, psychiatric or emotional conditions, or Parkinson's disease) or for 2 weeks after stopping the MAOI drug. If you do not know if your prescription drug contains an MAOI, ask a doctor or pharmacist before taking this product.
- with any other product containing acetaminophen (prescription or non-prescription). If you are not sure whether a drug contains acetaminophen, ask a doctor or pharmacist.
- if you are allergic to acetaminophen or any of the inactive ingredients in this product

Ask a doctor before use if you have

- liver disease
- heart disease
- diabetes
- high blood pressure
- thyroid disease
- trouble urinating due to an enlarged prostate gland
- cough accompanied by excessive phlegm (mucus)
- persistent or chronic cough such as occurs with smoking, asthma, or emphysema

Ask a doctor or pharmacist before use if you are

taking the blood thinning drug warfarin.

When using this product,

- do not use more than directed (see overdose warning)

Stop use and ask a doctor if

- redness or swelling is present
- new symptoms occur
- nervousness, dizziness, or sleeplessness occurs
- fever gets worse or lasts more than 3 days
- pain, cough or nasal congestion gets worse or lasts more than 7 days
- cough comes back or occurs with a fever, rash or headache that lasts. These could be signs of a serious condition.

If pregnant or breast-feeding,

ask a health professional before use.

Keep out of reach of children.

Overdose warning: Taking more than the recommended dose (overdose) may cause liver damage. In case of overdose, get medical help or contact a Poison Control Center (1-800-222-1222) immediately. Quick medical attention is critical for adults as well as for children even if you do not notice any signs or symptoms.

Directions

- do not use in infants
- do not exceed recommended dose (see overdose warning)
- use dosage cup provided
- tbsp = tablespoon, mL = milliliter

age | dose
adults and children 12 years and over | 2 tablespoons (30 mL) every 4 hours
children 4 to 11 years | do not use unless directed by a doctor
children under 4 years | do not use

Do not take more than 6 doses (12 tablespoons) in 24 hours.

Other information

- each 15 mL contains: sodium 8 mg
- store at room temperature

Inactive ingredients

acesulfame potassium, alcohol, citric acid, edetate disodium, FD&C blue 1, FD&C red 40, flavors, glycerin, maltitol solution, propylene glycol, purified water, sodium benzoate, sodium citrate

Questions or comments?

Call 1-877-753-3935 Monday-Friday 9AM-5PM EST

Principal Display Panel

Daytime

Flu Relief Therapy

SEVERE COLD

Pain Reliever / Fever Reducer - Acetaminophen

Cough Suppressant - Dextromethorphan HBr

Nasal Decongestant - Phenylephrine HCl

- Nasal Congestion • Sore Throat • Headache • Body Ache • Cough • Fever

*Compare to active ingredients in Theraflu®

Distributed by: SELECT BRAND DISTRIBUTORS

Pine Bluff, AR 71603 USA AC (870) 535-3635

Alcohol Content: 10%

Cherry Flavor

FL OZ (mL)

TAMPER EVIDENT: DO NOT USE IF PRINTED SAFETY SEAL ON THE CAP IS BROKEN OR MISSING.

Failure to follow the drug facts warnings could result in serious consequences.

PARENTS: Learn about teen medicine abuse www.StopMedicineAbuse.org

*This product is not manufactured or distributed by Novartis Consumer Health, Inc., owner of the registered trademark Theraflu® Daytime.

Product Label

Select Brand Flu Relief Therapy Daytime Severe Cold Cherry Liquid